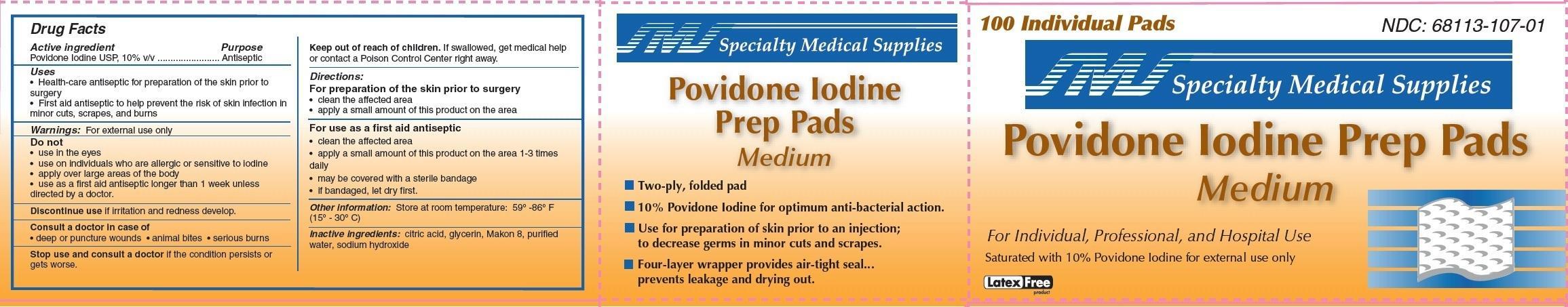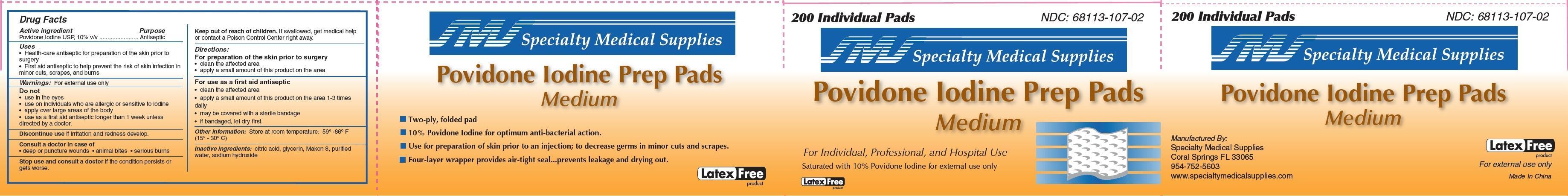 DRUG LABEL: POVIDONE-IODINE
NDC: 68113-107 | Form: SWAB
Manufacturer: Carribbean Medical Brokers d.b.a. Specialty Medical Supplies 
Category: otc | Type: HUMAN OTC DRUG LABEL
Date: 20130211

ACTIVE INGREDIENTS: POVIDONE-IODINE 0.10 g/1 1
INACTIVE INGREDIENTS: CITRIC ACID MONOHYDRATE; WATER; SODIUM HYDROXIDE

Povidone Iodine Prep Pad

Active ingredient

Povidone Iodine USP 10% v/v

Purpose

Antiseptic

Uses

- Health Care Antiseptic for preparation of the skin prior to surgery
- First Aid Antiseptic to help prevent infection in minor cuts, scrapes and burns

Warnings

For external use only

Do not

- use in the eyes
- use on individuals who are allergic or sensitive to iodine
- apply over large areas of the body
- use as a first aid antiseptic for longer than 1 week unless directed by a doctor.

Discontinue use if irritation and redness develop.

Consult a doctor in case of

- deep or puncture wounds
- animal bites
- serious burns

Stop use and consult a doctor

If condition persists or gets worse.

Keep out of reach of children.

If swallowed, get medical help or contact a Poison Control Center right away.

Directions:

For preparation of the skin prior to surgery

- clean the affected area
- apply a small amount of this product to the area

For use as a first aid antispetic

- clean the affected area
- apply a small amount of the product on the area 1-3 times daily
- may be covered with a sterile bandage
- If bandaged, let dry first.

Other Information:

Store at room temperature: 59o -86o F (15o - 30o C)

Inactive Ingredients

citric acid, glycerin, Makon 8, purified water, sodium hydroxide

Package Label

Specialty Medical Supplies
Povidone Iodine Prep Pads Medium
For Individual, Professional and Hospital Use
Saturated with 10% Povidone Iodine for external use only
100 Individual Pads
Latex free
Two ply folded pad
10% Povidone Iodine for optimum bacterial action
Use for preparation of the skin prior to an injection;
to decrease germs in minor cuts and scrapes.
Four layer wrapper provides air-tight seal...
prevents leakage and drying out.
Manufactured by
Specialty Medical Supplies
Coral Springs, FL 33065
954-752-5603
www.specialtymedicalsupplies.com
Made in China
Specialty Medical Supplies
Povidone Iodine Prep Pads Medium
For Individual, Professional and Hospital Use
Saturated with 10% Povidone Iodine for external use only
200 Individual Pads
Latex free
Two ply folded pad
10% Povidone Iodine for optimum bacterial action
Use for preparation of the skin prior to an injection;
to decrease germs in minor cuts and scrapes.
Four layer wrapper provides air-tight seal...
prevents leakage and drying out.
Manufactured by
Specialty Medical Supplies
Coral Springs, FL 33065
954-752-5603
www.specialtymedicalsupplies.com
Made in China